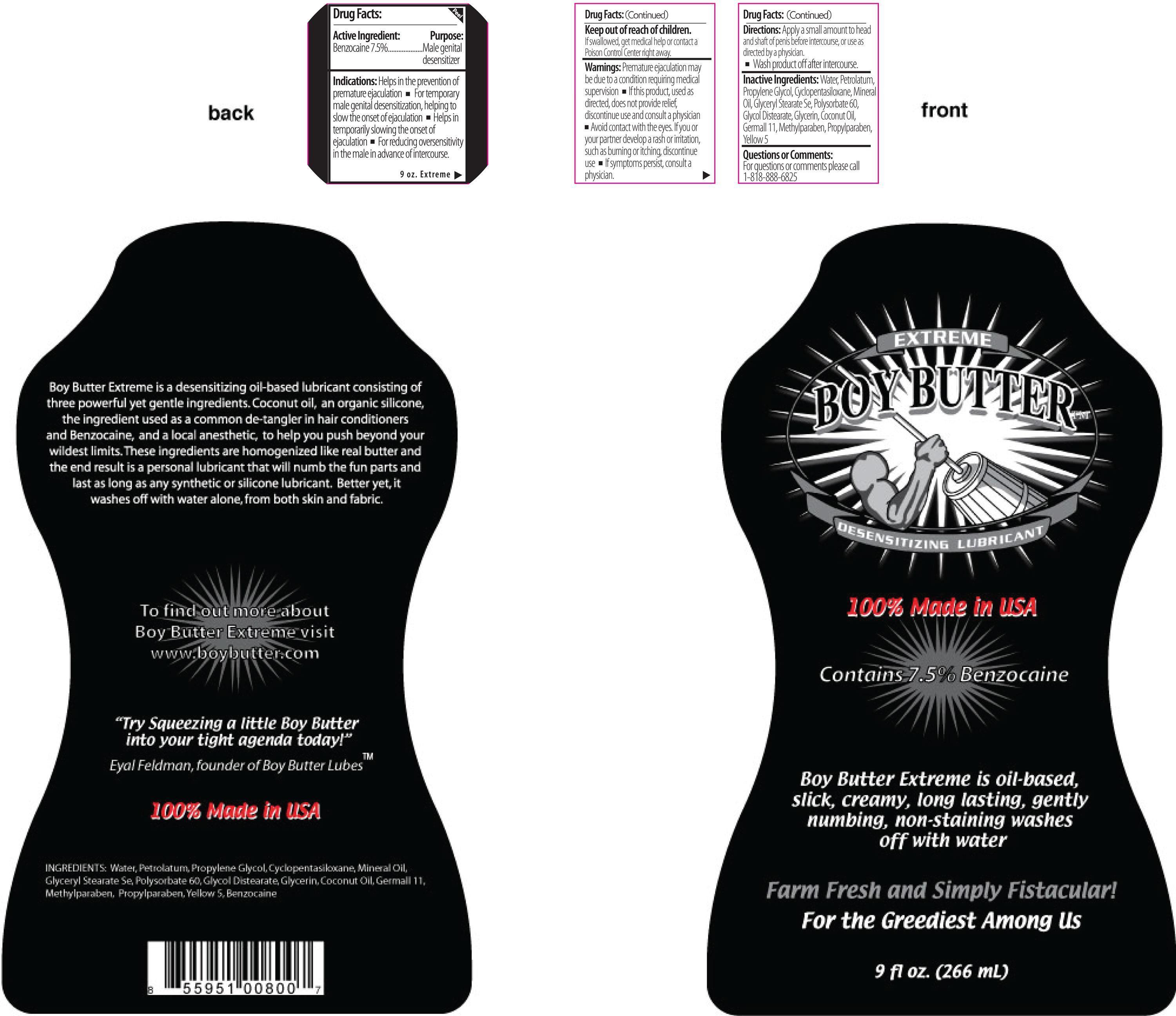 DRUG LABEL: Boy Butter
NDC: 24488-043 | Form: CREAM
Manufacturer: Boy Butter Lubes
Category: otc | Type: HUMAN OTC DRUG LABEL
Date: 20120925

ACTIVE INGREDIENTS: BENZOCAINE 71.9395789 mg/1 mL
INACTIVE INGREDIENTS: WATER; PETROLATUM; PROPYLENE GLYCOL; CYCLOMETHICONE 5; MINERAL OIL; GLYCERYL MONOSTEARATE; POLYSORBATE 60; GLYCOL DISTEARATE; GLYCERIN; COCONUT OIL; DIAZOLIDINYL UREA; METHYLPARABEN; PROPYLPARABEN; FD&C YELLOW NO. 5

Drug Facts:

Active Ingredient:

Benzocaine 7.5%

Purpose

Male genital desensitizer

Indications:

Helps in the prevention of premature ejaculation.

- For temporary male genital desensitization, helping to slow the onset of ejaculation
- Helps in temporarily slowing the onset of ejaculation
- For reducing oversensitivity in the male in advancer of intercourse.

Keep out of reach of children

If swallowed, get medical help or contact a
Poison Control Center right away.

Warnings:

Premature ejaculation may be due to a condition requiring medical supervision.

- If this product, used as directed, does not provide relief, discontinue use and consult a physician
- Avoid contact with the eye. If you or your partner develop a rash or irritation, such as burning or itching, discontinue use
- If symptoms persist, consult a physician.

Directions:

Apply a small amount to head and shaft of penis before intercourse, or use as directed by a physician

- Wash product off after intercourse

Inactive Ingredients:

Water, Petrolatum, Propylene Glycol, Cyclopentasiloxane, Mineral Oil, Glyceryl Stearate Se, Polysorbate 60, Glycol Distearate, Coconut Oil, Germall 11, Methyparaben, Propylparaben, Yellow 5

Questions or Comments:

For questions or comments, please call 1-818-888-6825

PACKAGE LABEL

Placeholder Text